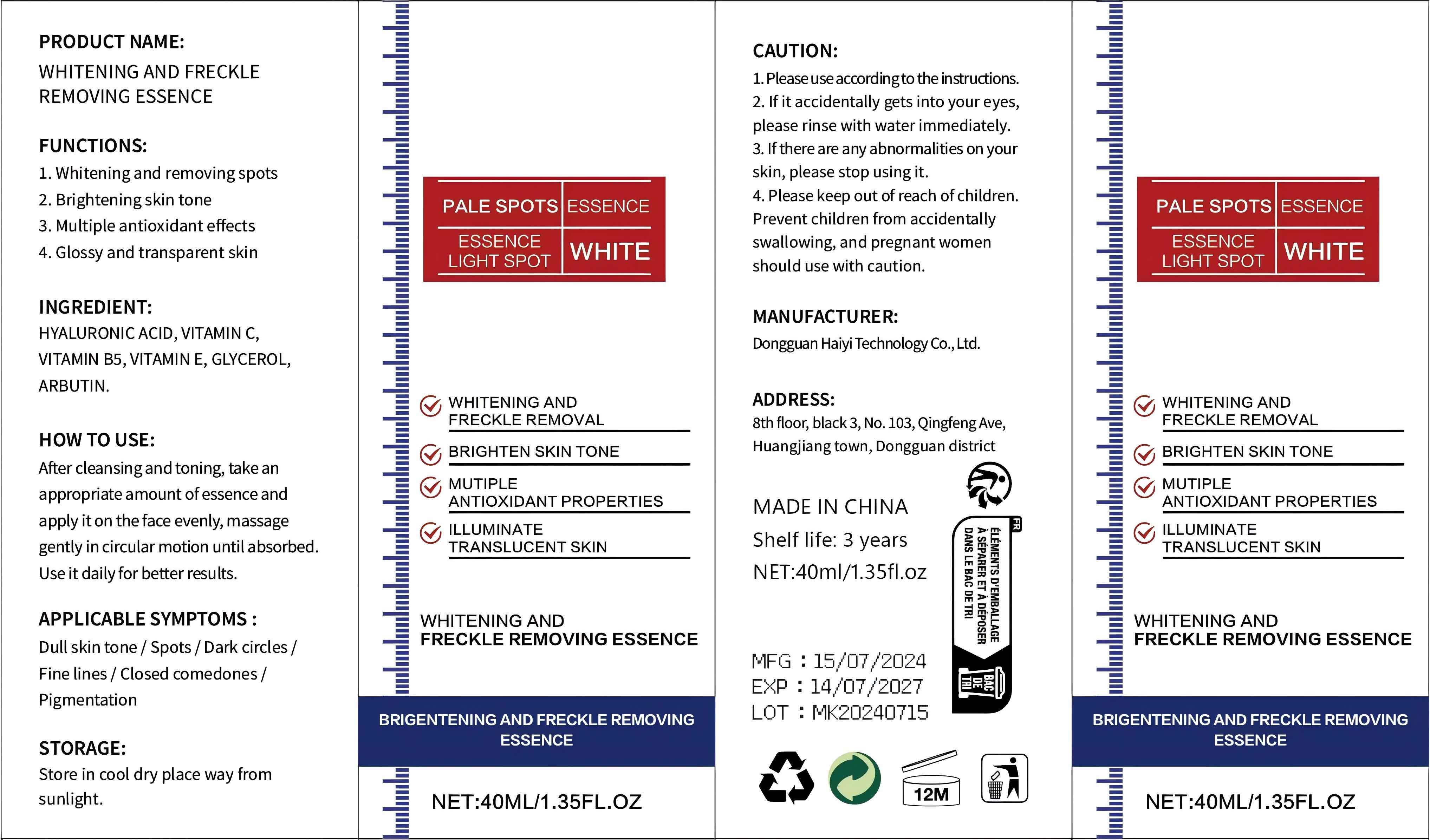 DRUG LABEL: WHITENING AND FRECKLE REMOVING ESSENCE
NDC: 84732-078 | Form: LIQUID
Manufacturer: Dongguan Haiyi Technology Co.,Ltd.
Category: otc | Type: HUMAN OTC DRUG LABEL
Date: 20241031

ACTIVE INGREDIENTS: HYALURONIC ACID 1 mg/40 mL
INACTIVE INGREDIENTS: ARBUTIN; ASCORBIC ACID; .ALPHA.,.ALPHA.'-DIGLYCEROL; .ALPHA.-TOCOPHEROL; PANTOTHENIC ACID

Active ingredient

HYALURONIC ACID

Inactive ingredient

VITAMIN C,VITAMIN B5, VITAMIN E, GLYCEROL,ARBUTIN.

Purpose section

1.Whitening and removing spots

2. Brightening skin tone

3. Multiple antioxidant effects

4. Glossy and transparent skin

Warning

1. Please use according to the instructions.

2. lf it accidentally gets into your eyes,please rinse with water immediately.

3. lfthere are any abnormalities on yourskin, please stop using it.

4. Please keep out of reach ofchildren.Prevent children from accidentallyswallowing, and pregnant womenshould use with caution.

stop use

This product may cause allergic reactions in asmall number of people.
lf youexperience any discomfort,please stop using it immediately.

not use

Not suitable for use by children, pregnantor breast feeding people.

OUT OF CHILDREN

KEEP THE PRODUCT OUT OF REACH OF CHILDREN to

HOW TO USE

After cleansingand toning, take anappropriate amount ofessence andapply it on the face evenly, massagegently in circular motion until absorbed.Use it daily for better results.

Dosage

take an appropriateamount,Use 2-3 times a week